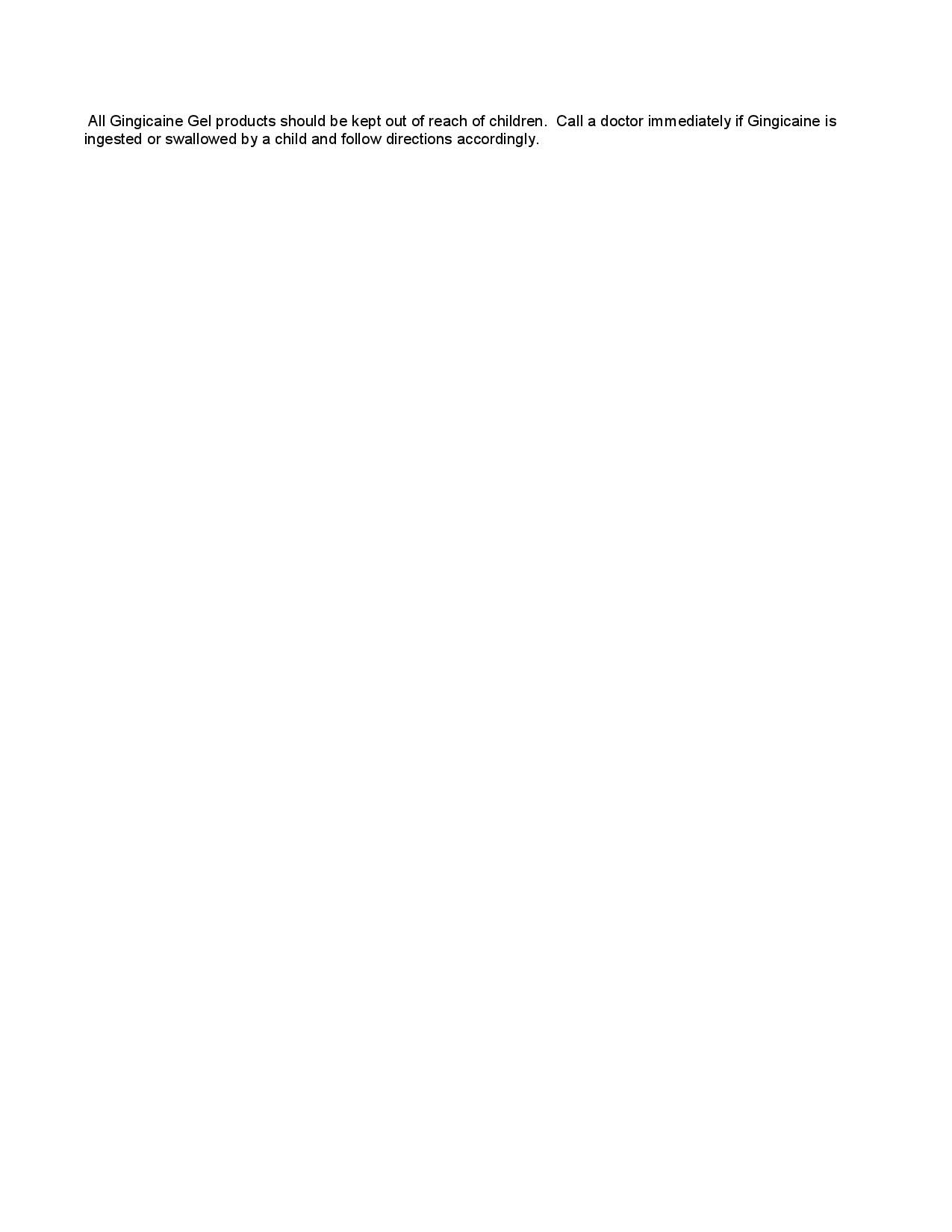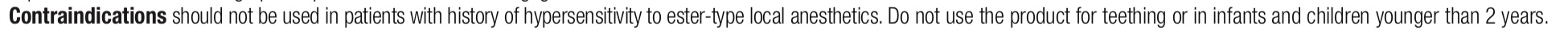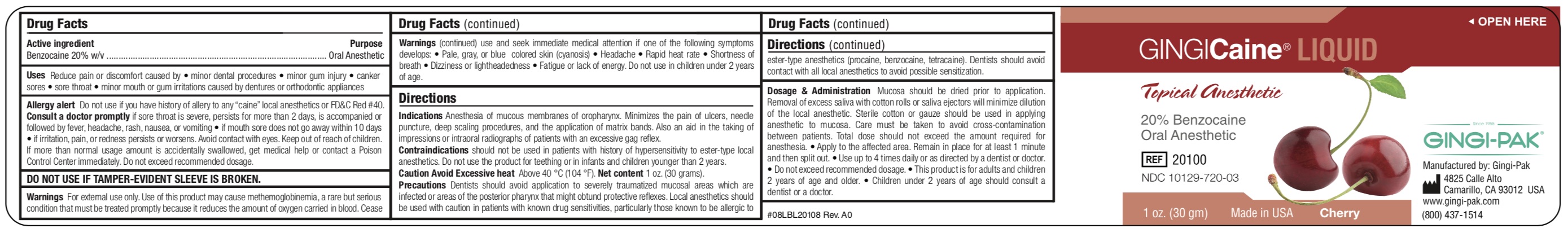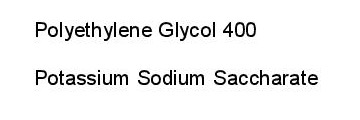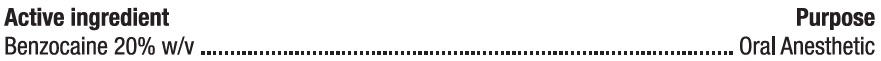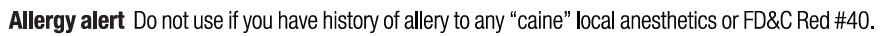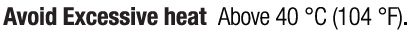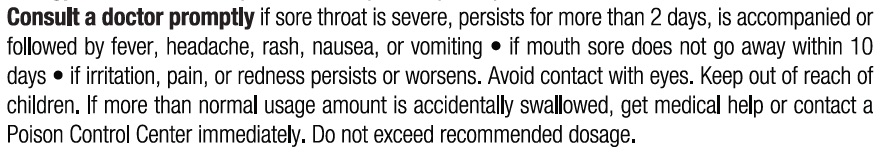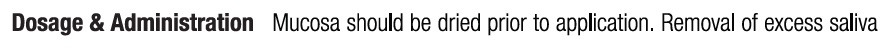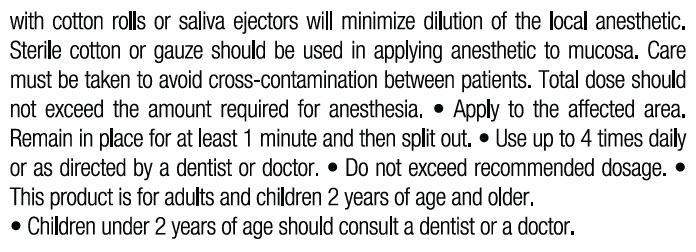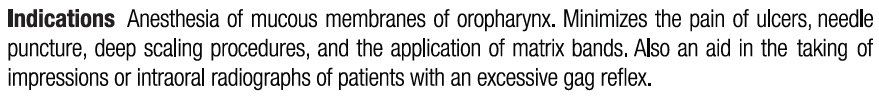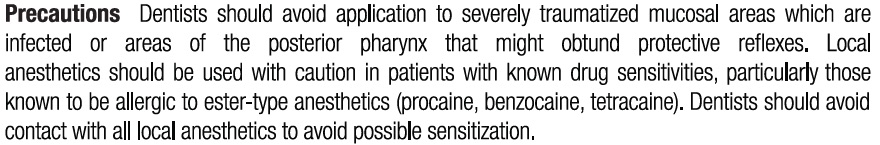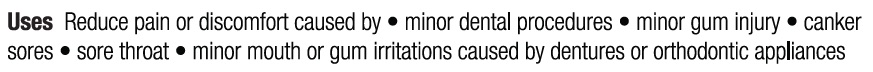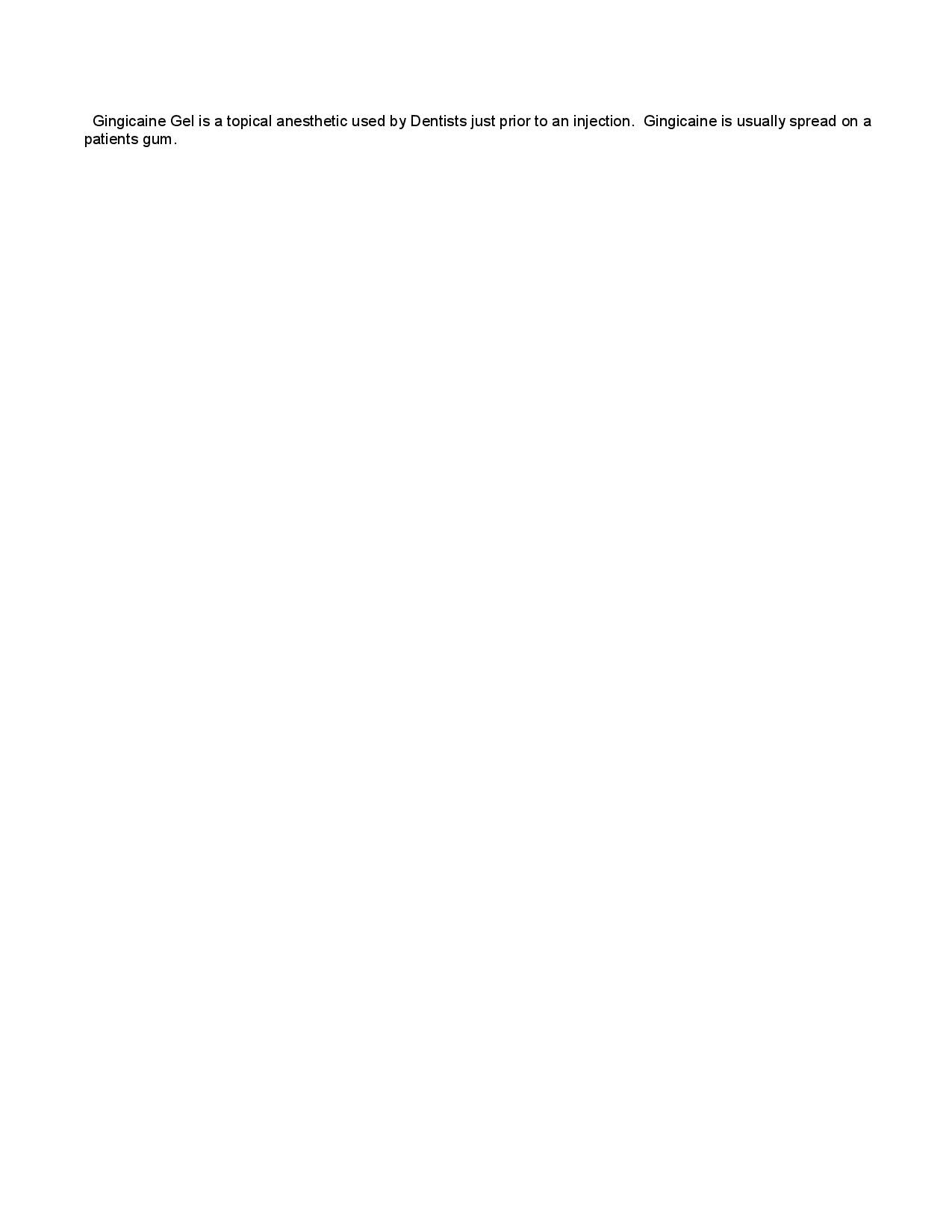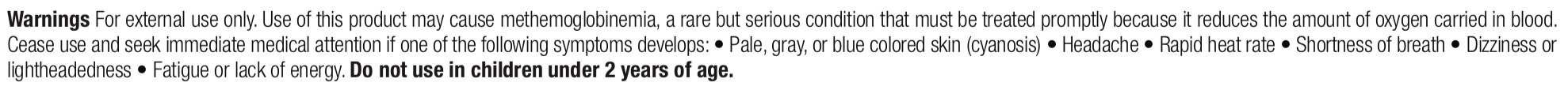 DRUG LABEL: GingiCaine Liquid, Cherry
NDC: 10129-720 | Form: LIQUID
Manufacturer: Gingi-Pak a Division of the Belport
Category: otc | Type: HUMAN OTC DRUG LABEL
Date: 20211209

ACTIVE INGREDIENTS: BENZOCAINE 200 mg/1 1
INACTIVE INGREDIENTS: POLYETHYLENE GLYCOL 400 785 mg/1 1; POTASSIUM SODIUM SACCHARATE 20 mg/1 1

GingiCaine Liquid, Cherry